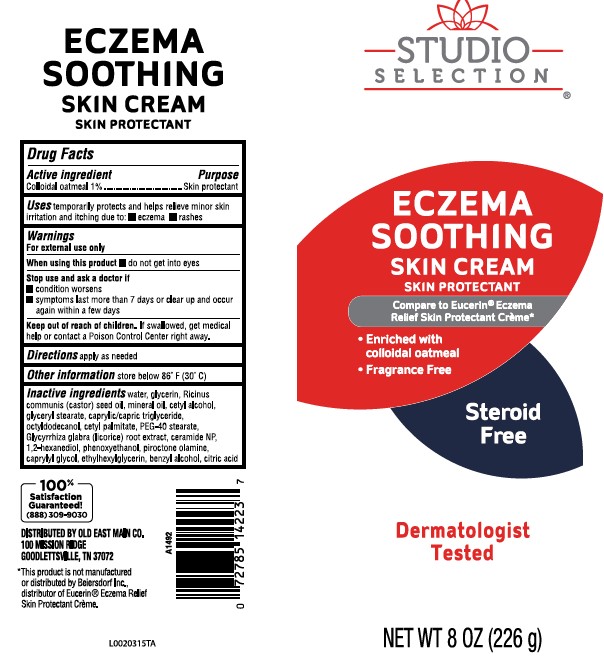 DRUG LABEL: Eczema Relief
NDC: 55910-653 | Form: OINTMENT
Manufacturer: Old East Main Co.
Category: otc | Type: HUMAN OTC DRUG LABEL
Date: 20260302

ACTIVE INGREDIENTS: OATMEAL 10 mg/11 g
INACTIVE INGREDIENTS: WATER; GLYCERIN; CASTOR OIL; MINERAL OIL; CETYL ALCOHOL; GLYCERYL STEARATE SE; MEDIUM-CHAIN TRIGLYCERIDES; OCTYLDODECANOL; CETYL PALMITATE; PEG-40 STEARATE; GLYCYRRHIZA GLABRA; CERAMIDE NP; 1,2-HEXANEDIOL; PHENOXYETHANOL; PIROCTONE OLAMINE; CAPRYLYL GLYCOL; ETHYLHEXYLGLYCERIN; BENZYL ALCOHOL; CITRIC ACID ACETATE

Studio Selection 289.000/289AA
Eczema Soothing Skin Cream

Claims

ECZEMA

SOOTHING

SKIN CREAM

SKIN PROTECTANT

Active Ingredient

Colloidal oatmeal 1%

Purpose

Skin protectant

Uses

temporarily protects and helps relieve minor skin irritation and itching due to:

- eczema
- rashes

Warnings

for external use only

When using this product

- do not get into eyes

Stop use and ask a doctor if

- condition worsens
- symptoms last more than 7 days or clear up and occur again within a few days

Keep out of reach of children.

If swallowed, get medical help or contact a Poison Control Center right away.

Directions

- apply as needed

other information

store below 86°F (30°C)

Inactive ingredients

water, glycerin, Ricinus communis (castor) seed oil, mineral oil, cetyl alcohol, glyceryl stearate, caprylic/capric triglyceride, octyldodecanol, cetyl palmitate, PEG-40 stearate, Glycyrrhiza glabra (licorice) root extract, ceramide NP, 1,2-hexanediol, phenoxyethanol, piroctone olamine, caprylyl glycol, ethylhexylglycerin, benzyl alcohol, citric acid

Adverse reactions

100% Satisfaction Guaranteed!

(888)309-9030

DISTRIBUTED BY OLD EAST MAIN CO.

100 MISSION RIDGE

GOODLETTSVILLE, TN 37072

Disclaimer

*This product is not manufactured or distributed by Beiersdorf Inc., distributor of EucerinEczema Relief Skin Protectant Creme.

principal display panel

STUDIO SELECTION®

ECZEMA

SOOTHING

SKIN CREAM

SKIN PROTECTANT

Compare to Eucerin®Eczema Relief Skin Protectant Creme*

- Enriched with colloidal oatmeal
- Fragrance Free

Steroid Free

Dermatologist Tested

NET WT 8 OZ (226 g)